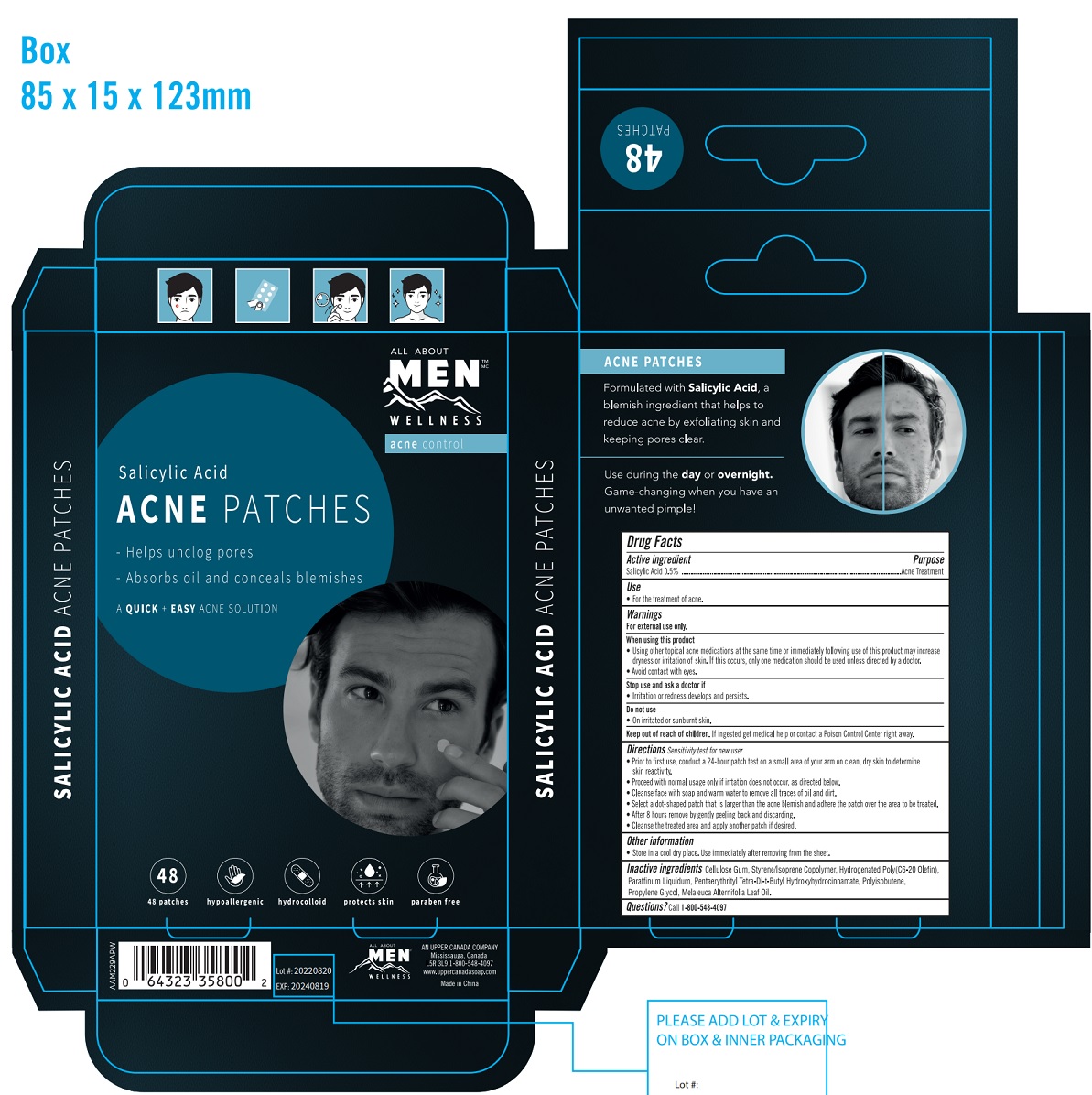 DRUG LABEL: Salicylic Acid Acne Patches
NDC: 69139-120 | Form: PATCH
Manufacturer: YIWU HAODING MEDICAL CO.,LTD
Category: otc | Type: HUMAN OTC DRUG LABEL
Date: 20220915

ACTIVE INGREDIENTS: SALICYLIC ACID 0.5 mg/100 mg
INACTIVE INGREDIENTS: CARBOXYMETHYLCELLULOSE SODIUM; styrene; HYDROGENATED C6-20 POLYOLEFIN (100 CST); MINERAL OIL; PENTAERYTHRITOL TETRAKIS(3-(3,5-DI-TERT-BUTYL-4-HYDROXYPHENYL)PROPIONATE); POLYISOBUTYLENE (1300 MW); PROPYLENE GLYCOL; TEA TREE OIL

Salicylic Acid Patches

ACTIVE INGREDIENT

Salicylic Acid 0.5%

PURPOSE

Acne Treatment

WARNINGS

For external use only

WHEN USING

- Using other topical acne medications at the same time or immediately following use of this product may increase dryness or irritation of skin. If this occurs, only one medication should be used unless directed by a doctor.
- Avoid contact with eyes.

Stop use and ask a doctor

- if irritation or redness develops and persists.

DO NOT USE

- On irritated or sunburnt skin.

Keep out of reach of children. If ingested, get medical help or contact Poison Control Center right away.

Other

- Store in a cool dry place. Use immediately after removing from the sheet.

INDICATIONS AND USAGE

Use for the treatment of acne

QUESTIONS

Question? 1-800-548-4097

Directions

- Sensitivity test for new user
- Prior to first use, conduct a 24-hour patch test on a small area of your arm on clean, dry skin to determine skin reactivity.
- Proceed with normal usage only if irritation does not occur, as directed below.
- Cleanse face with soap and warm water to remove all traces of oil and dirt.
- Select a dot-shaped patch that is larger than the acne blemish and adhere the patch over the area to be treated.
- After 8 hours remove by gently peeling back and discarding.
- Cleanse the treated area and apply another patch if desired.

INACTIVE INGREDIENT

Cellulose Gum, Styrene/Isoprene Copolymer, Hydrogenated Poly (C6-20 Olefin), Paraffinum Liquidum, Pentaerthrityl Tetra-Di-t-Butyl Hydroxyhydrocinnamate, Polyisobutene, Propylene Glycol, Melaleuca Alternifolia Leaf Oil.